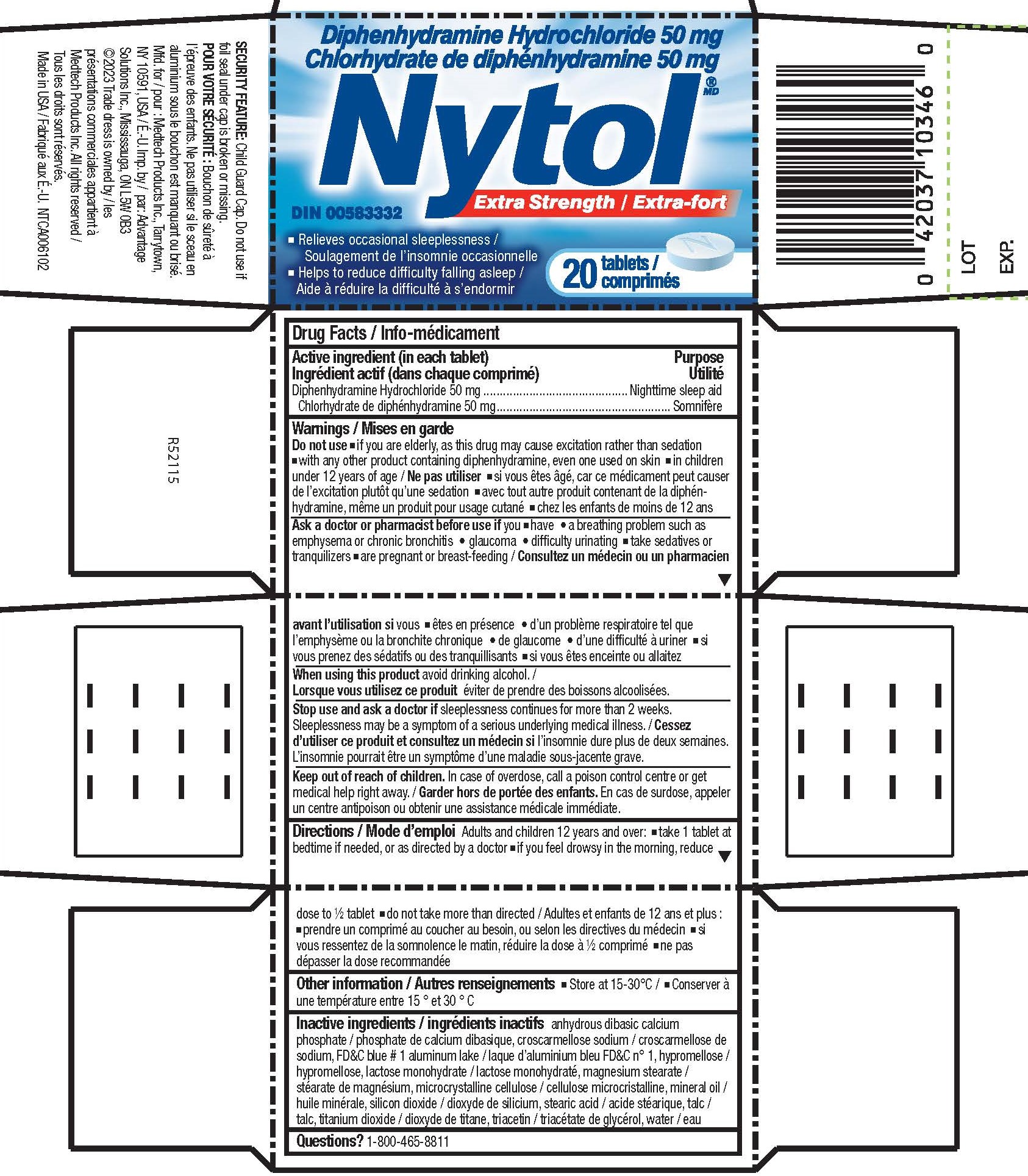 DRUG LABEL: Diphenhydramine Hydrochloride
NDC: 10267-4381 | Form: TABLET, FILM COATED
Manufacturer: Contract Pharmacal Corp.
Category: otc | Type: HUMAN OTC DRUG LABEL
Date: 20231130

ACTIVE INGREDIENTS: DIPHENHYDRAMINE HYDROCHLORIDE 50 mg/1 1
INACTIVE INGREDIENTS: LACTOSE MONOHYDRATE; MAGNESIUM STEARATE; LIGHT MINERAL OIL; DIBASIC CALCIUM PHOSPHATE DIHYDRATE; SILICON DIOXIDE; STEARIC ACID; TALC; MICROCRYSTALLINE CELLULOSE; TITANIUM DIOXIDE; CROSCARMELLOSE SODIUM; FD&C BLUE NO. 1; HYPROMELLOSES; TRIACETIN

4381- Export